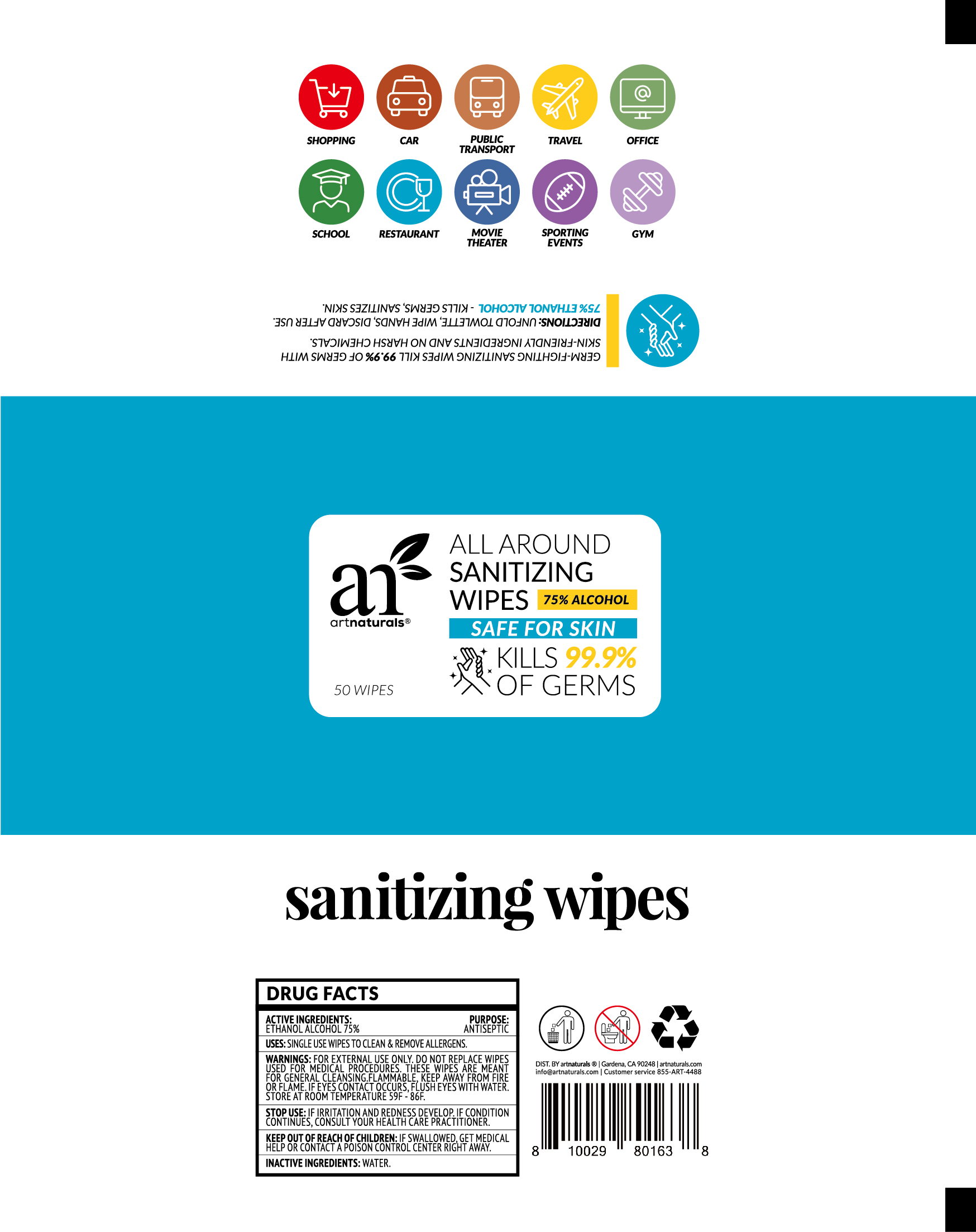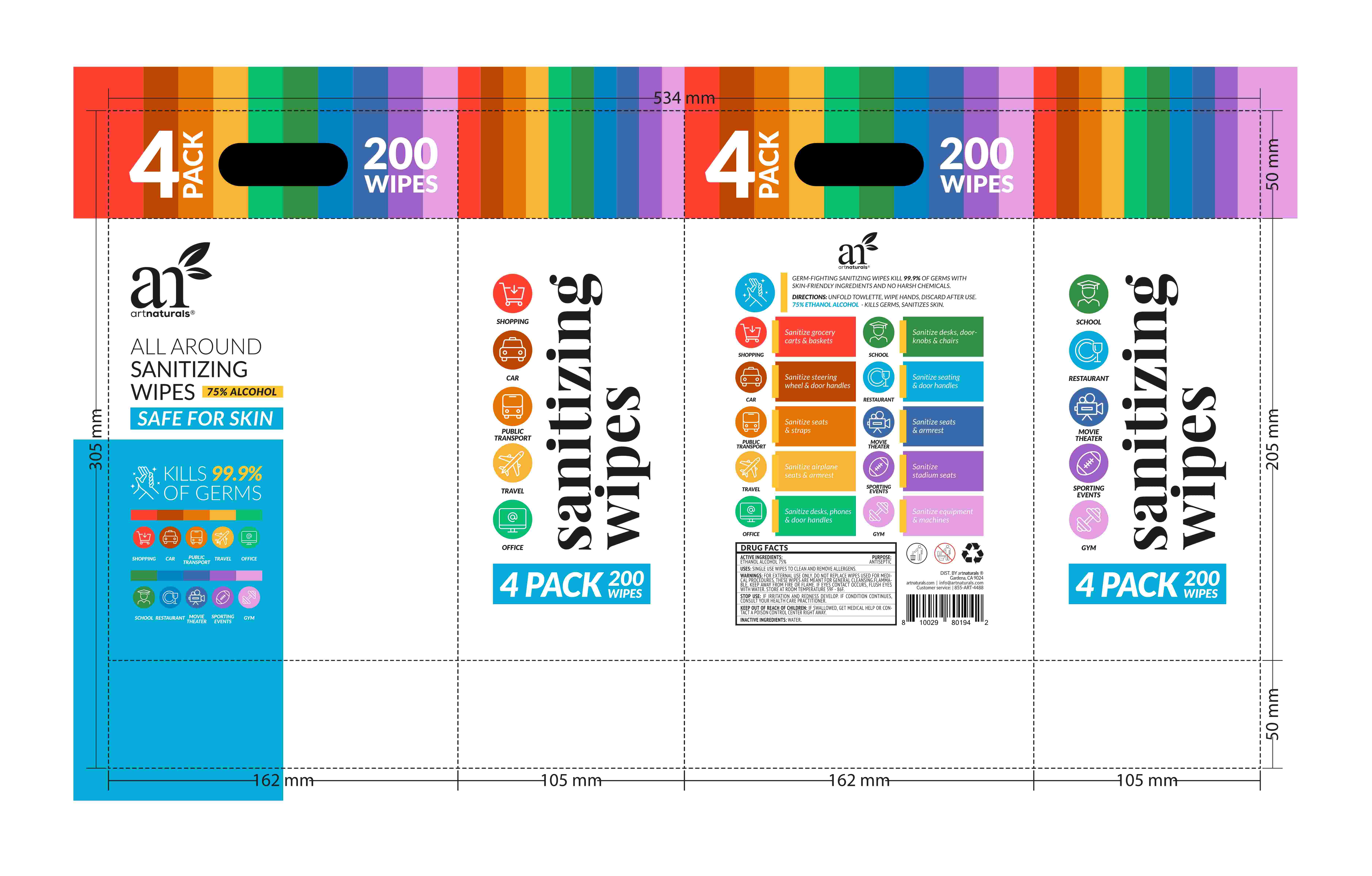 DRUG LABEL: Sanitizing wipes
NDC: 42129-005 | Form: CLOTH
Manufacturer: Fustin(Xiamen) Commodity Co., ltd
Category: otc | Type: HUMAN OTC DRUG LABEL
Date: 20200616

ACTIVE INGREDIENTS: ALCOHOL 75 1/100 1
INACTIVE INGREDIENTS: WATER

Sanitizing wipes

Active Ingredient(s)

Ethanol Alcohol 75%

Purpose

/

Use

SINGLE USE WIPES TO CLEAN & REMOVE ALLERGENS

Warnings

FOR EXTERNAL USE ONLY. DO NOT REPLACE WIPES FOR GENERAL CLEANSING. FLAMMABLE. KEEP AWAY FROM FIRE OR FLAME. IF EYES CONTACT OCCURS. FLUSH EYES WITH WATEISTORE AT ROOM TEMPERATURE 59F-86F

Do not use

/

WHEN USING

/

Stop use and ask a doctor if irritation or rash occurs. These may be signs of a serious condition.

Keep out of reach of children. If swallowed, get medical help or contact a Poison Control Center right away.

Directions

DIRECTIONS : UNFOLD TOWLETTE, WIPE HANDS, DISCARD AFTER USE. 75% ETHANOL ALCOHOL-KILLS GERMS SANITIZES SKIN

Inactive ingredients

water